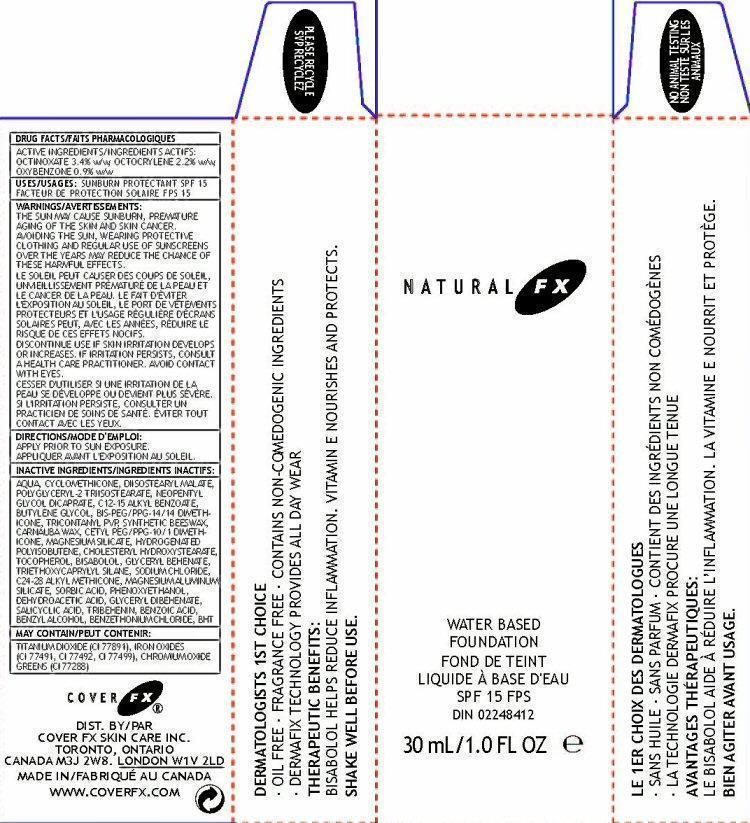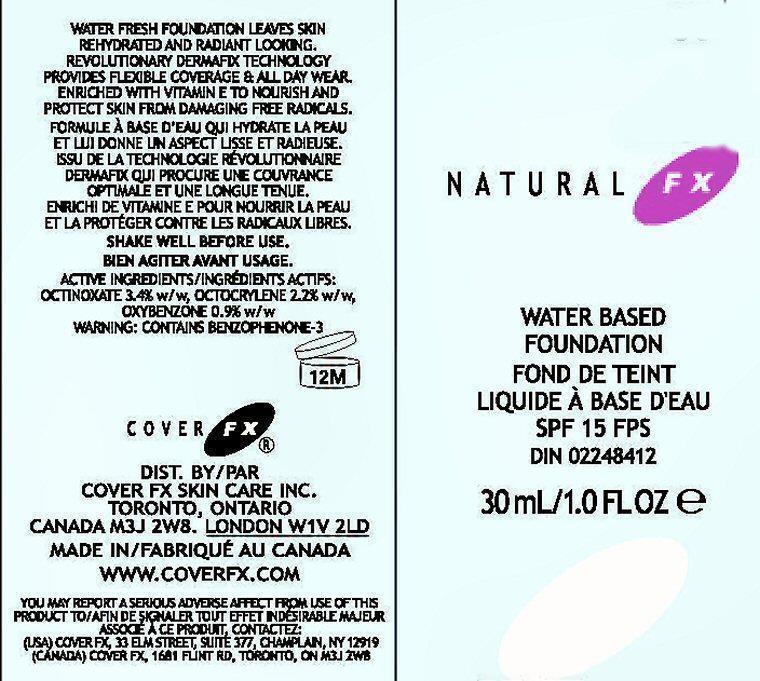 DRUG LABEL: Natural  FX
NDC: 68327-002 | Form: CREAM
Manufacturer: Cover FX Skin Care, Inc.
Category: otc | Type: HUMAN OTC DRUG LABEL
Date: 20130220

ACTIVE INGREDIENTS: OCTINOXATE 3.4 g/100 mL; OCTOCRYLENE 2.2 g/100 mL; OXYBENZONE 0.9 g/100 mL
INACTIVE INGREDIENTS: WATER; CYCLOMETHICONE; DIISOSTEARYL MALATE; NEOPENTYL GLYCOL DICAPRATE; ALKYL (C12-15) BENZOATE; BUTYLENE GLYCOL; TRIACONTANYL PVP (WP-660); CARNAUBA WAX; CETYL PEG/PPG-10/1 DIMETHICONE (HLB 5); MAGNESIUM SILICATE; HYDROGENATED POLYBUTENE (370 MW); CHOLESTERYL HYDROXYSTEARATE; TOCOPHEROL; LEVOMENOL; GLYCERYL DIBEHENATE; TRIETHOXYCAPRYLYLSILANE; SODIUM CHLORIDE; MAGNESIUM ALUMINUM SILICATE; SORBIC ACID; PHENOXYETHANOL; DEHYDROACETIC ACID; GLYCERYL DIBEHENATE; SALICYLIC ACID; TRIBEHENIN; BENZOIC ACID; BENZYL ALCOHOL; BENZETHONIUM CHLORIDE; BUTYLATED HYDROXYTOLUENE; TITANIUM DIOXIDE; FERRIC OXIDE RED; CHROMIC OXIDE

Active Ingredients Section

DRUG FACTS: ACTIVE INGREDIENTS: OCTINOXATE 3.4% w/w, OCTOCRYLENE 2.2% w/w, OXYBENZONE 0.9% w/w

Purpose Section

WATER FRESH FOUNDATION LEAVES SKIN REHYDRATED AND RADIANT LOOKING. REVOLUTIONARY DERMAFIX TECHNOLOGY PROVIDES FLEXIBLE COVERAGE AND ALL DAY WEAR. ENRICHED WITH VITAMIN E TO NOURISH AND PROTECT SKIN FROM DAMAGING FREE RADICALS.

Keep Out Of Reach Of Children Section

Enter section text here

Uses

USES: SUNBURN PROTECTANT SPF 15

THERAPEUTIC BENEFITS: BISBOLOL HELPS REDUCE INFLAMMATION. VITAMIN E NOURISHES AND PROTECTS.

DERMATOLOGISTS 1ST CHOICE OIL FREE FRAGRANCE FREE CONTAINS NON-COMEDOGENIC INGREDIENTS DERMAFIX TECHNOLOGY PROVIDES ALL DAY WEAR

Warning Section

WARNINGS:

THE SUN MAY CAUSE SUNBURN, PREMATURE AGING OF THE SKIN AND SKIN CANCER. AVOIDING THE SUN, WEARING PROTECTIVE CLOTHING AND REGULAR USE OF SUNSCREEN OVER THE YEARS MAY REDUCE THE CHANCE OF THESE HARMFUL EFFECTS.

DISCONTINUE USE IF SKIN IRRITATION DEVELOPS OR INCREASES. IF SKIN IRRITATION PERSISTS, CONTACT A HEALTH CARE PRACTITIONER. AVOID CONTACT WITH EYES.

Directions

APPLY PRIOR TO SUN EXPOSURE.

Inactive Ingredients

WATER, CYCLOMETHICONE, DIIOSTEARYL MALATE,POLYGLYCERYL-2 TRIISOSTEARATE, NEOPENTYL GLYCOL DICAPRATE, C12-15 ALKYL BENZOATE, BUTYLENE GLYCOL, BIS-PEG/PPG-14/14 DIMETHICONE,TRICONTANYL PVP, SYNTHETIC BEESWAX,CARNAUBA WAX, CETYL PEG/PPG-10/1 DIMETHICONE, MAGNESIUM SILICATE, HYDROGENATED POLYISOBUTENE, CHOLESTERYL HYDROXYSTEARATE,
TOCOPHEROL, BISABOLOL, GLYCERYL BEHENATE, TRIETHOXYCAPRYLYL SILANE, SODIUM CHLORIDE,C24-28 ALKYL METHICONE, MAGNESIUM ALUMINUM SILICATE, SORBIC ACID, PHENOXYETHANOL, DEHYDROACETIC ACID, GLYCERYL DIBEHENATE,
SALICYCLIC ACID, TRIBEHENIN, BENZOIC ACID, BENZYL ALCOHOL, BENZETHONIUM CHLORIDE, BHT

MAY CONTAIN:

TITANIUM DIOXIDE (CI 77891), IRON OXIDES (CI 77491, CI 77492, CI 77499), CHROMIUM OXIDE GREENS (CI 77288)

Product Label

NATURAL FX

WATER BASED
FOUNDATION
SPF 15 FPS
DIN 02248412

30Ml/1.0 fl oz

WATER FRESH FOUNDATION LEAVES SKIN REHYDRATED AND RADIENT LOOKING. REVOLUUTIONARY DERMAFIX TECHNOLOGY PROVIDES FLEXIBLE COVERAGE AND ALL DAY WEAR. ENRICHED WITH VITAMIN e TO NOURISH AND PROTECT SKIN FROM DAMAGING FREE RADICALS.

WARNING: CONTAINS BENZOPHENONE-3 PLEASE RECYCLE

COVER FX
DIST. BY/PAR
COVER FX SKIN CARE INC.
TORONTO, ONTARIO
CANADA M3J 2W8. LONDON W1V 2LD
MADE IN/FABRIQUÉ AU CANADA
WWW.COVERFX.COM

DERMATOLOGISTS 1ST CHOICE
∙ OIL FREE ∙ FRAGRANCE FREE ∙ CONTAINS NON-COMEDOGENIC INGREDIENTS
∙ DERMAFIX TECHNOLOGY PROVIDES ALL DAY WEAR
THERAPEUTIC BENEFITS:
BISABOLOL HELPS REDUCE INFLAMMATION. VITAMIN E NOURISHES AND PROTECTS.
SHAKE WELL BEFORE USE.

YOU MAY REPORT A SERIOUS ADVERSE AFFECT FROM USE OF THIS PRODUCT TO (USA) COVER FX 33 ELM STREET, SUITE 377, CHAMPLANE, NY 12919

(CANADA) COVER FX, 1681 FLINT RD, TORONTO, ON M3J 2W8